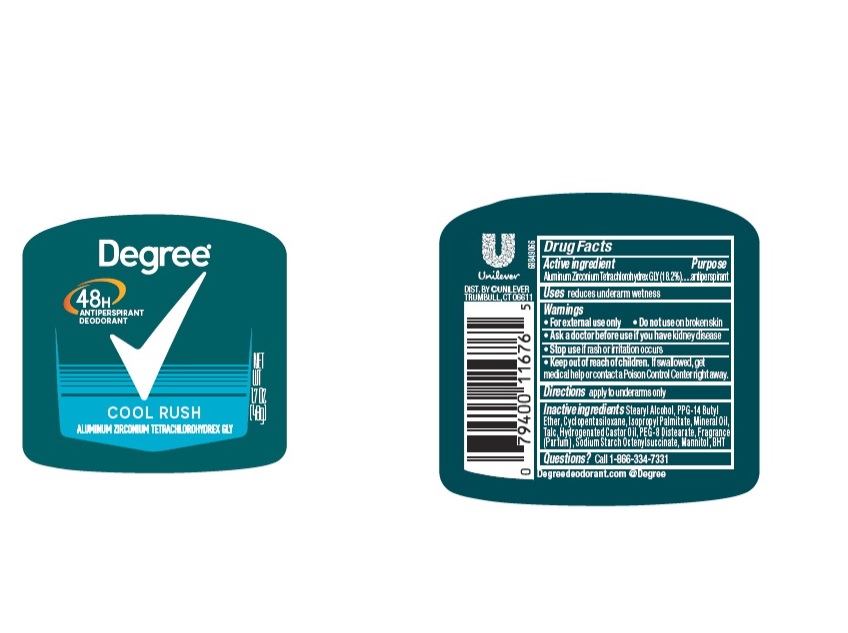 DRUG LABEL: Degree
NDC: 64942-1997 | Form: STICK
Manufacturer: Conopco Inc. d/b/a/ Unilever
Category: otc | Type: HUMAN OTC DRUG LABEL
Date: 20241108

ACTIVE INGREDIENTS: ALUMINUM ZIRCONIUM TETRACHLOROHYDREX GLY 18.2 g/100 g
INACTIVE INGREDIENTS: MINERAL OIL; HYDROGENATED CASTOR OIL; CYCLOMETHICONE 5; BUTYLATED HYDROXYTOLUENE; MANNITOL; PEG-8 DISTEARATE; TALC; ISOPROPYL PALMITATE; PPG-14 BUTYL ETHER; STEARYL ALCOHOL

Degree Cool Rush 48H Antiperspirant Deodorant

Drug Facts

Active ingredient

Aluminum Zirconium Tetrachlorohydrex GLY (18.2 %)

Purpose

antiperspirant

Uses

reduces underarm wetness

Warnings

• For external use only.
• Do not use on broken skin .
• Ask a doctor before use if you have kidney disease.
• Stop use if rash or irritation occurs.

• Keep out of reach of children.

If swallowed, get medical help or contact a Poison Control Center right away.

Directions

apply to underarms only

Inactive ingredients

Stearyl Alcohol, PPG-14 Butyl Ether, Cyclopentasiloxane, Isopropyl Palmitate, Mineral Oil, Talc, Hydrogenated Castor Oil, PEG-8 Distearate, Fragrance (Parfum), Sodium Starch Octenylsuccinate, Mannitol, BHT

Questions?

Call toll-free 1-866-334-7331